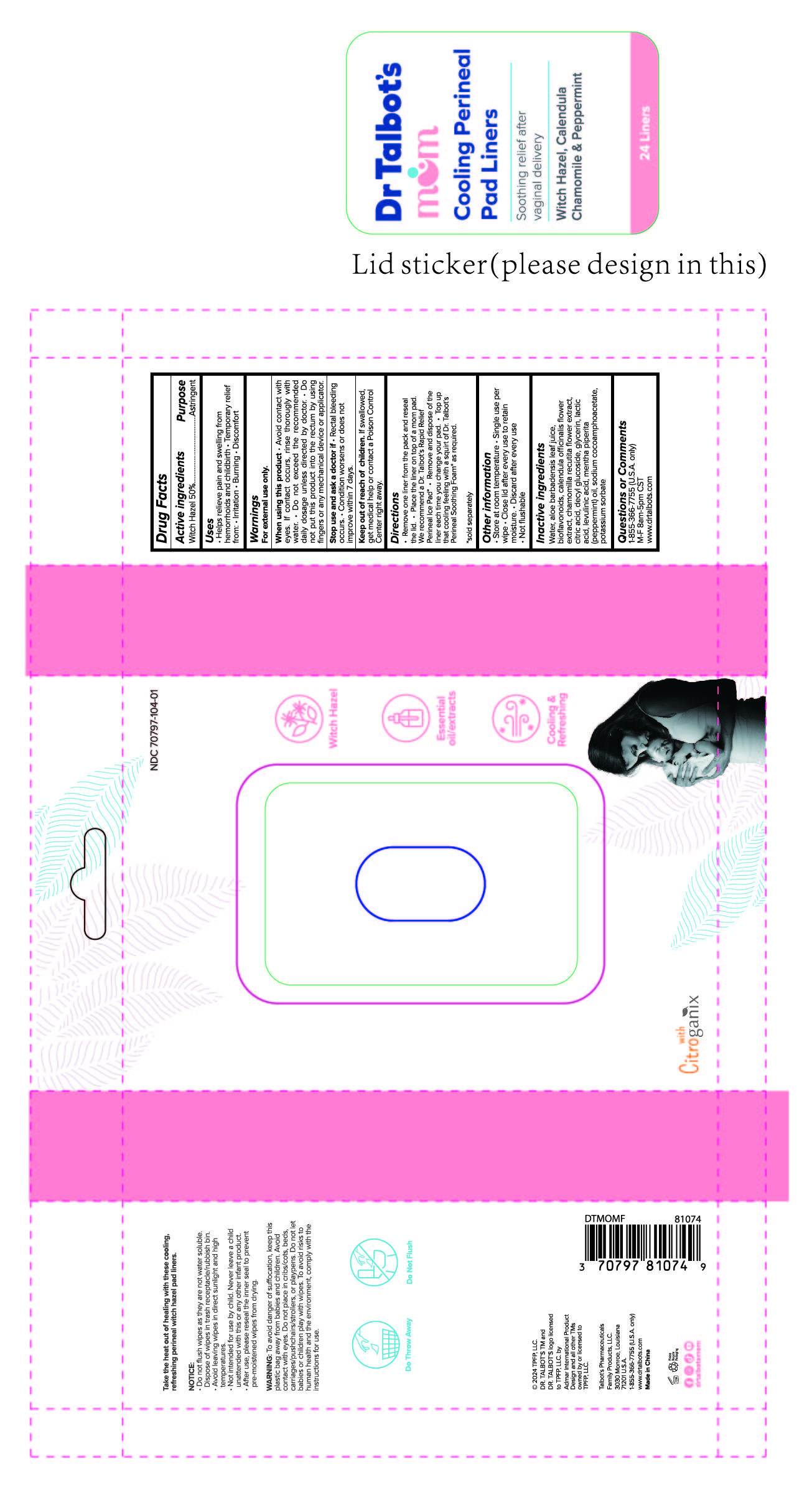 DRUG LABEL: Dr Talbots Cooling Perineal Pad
NDC: 70797-104 | Form: LIQUID
Manufacturer: Talbot's Pharmaceuticals family Products, LLC.
Category: otc | Type: HUMAN OTC DRUG LABEL
Date: 20250314

ACTIVE INGREDIENTS: WITCH HAZEL 0.5 g/1 g
INACTIVE INGREDIENTS: POTASSIUM SORBATE 0.4 g/1 g

WARNINGS FOR EXTERNAL USE ONLY

For external use only:

- Avoid contact with eye. If contact occurs, rinse thoroughly with water.
- Do not exceed the recommended daily dosage unless directed by doctor.
- Do not put this product in the rectum by using fingers or any mechanical device or applicator.

ACTIVE INGREDIENTS

- WITCH HAZEL 50% - ASTRINGENT

INACTIVE INGREDIENTS

- Water
- aloe barbadensis leaf juice
- bioflavonoids
- calendula officinalis flower extract
- citric acid
- decyl glucoside
- glycerin
- lactic acid
- levulinic acid
- mentha piperita (peppermint) oil
- sodium cocoamphoacetate
- potassium sorbate

KEEP OUT OF REACH OF CHILDREN

If swallowed, get medical help or contract a Poison Control CEnter right away.

STOP USE AND ASK A DOCTOR IF

- Rectal bleeding occurs.

- Condition worsens or does not improves within 7 days.

OTHER INFORMATION

- Store at room temerature
- single use per wipe
- close lid after every use to retain moisture
- Not flushable

USES

- Helps relieve pain and swelling from hemmorrhoids and children.
- Temperoray relief from irritation.
- Burning
- Discomfort

DOSAGE AND ADMINISTRATION

- Remove one liner from the pack and reseal the lid.
- Place the liner on top of mom pad.
- We recommend a Dr Talbot's Rapid Relief Perineal Pad.
- Remove and dispose of the liner each time you change your pad.
- Top up that cooling feeling with a squirt of DR Talbot's Perineal Soothing Foam as required.

INDICATION & USAGE SECTION

- ASTRINGENT
- HELPS RELIEVES PAIN & SWELLING FROM HEMORRHOIDS & CHILDBIRTH
- TEMPORARY RELIEF FROM IRRITATION, BURNING, DISCOMFORT

INDICATION AND USAGE SECTION

- Helps relieve pain and swelling from hemorrhoids and childbirth.
- temporary relief from Irritation, Burning, Discomfort.

COOLING PERINEAL PAD LINER

- SOOTHING RELIEF